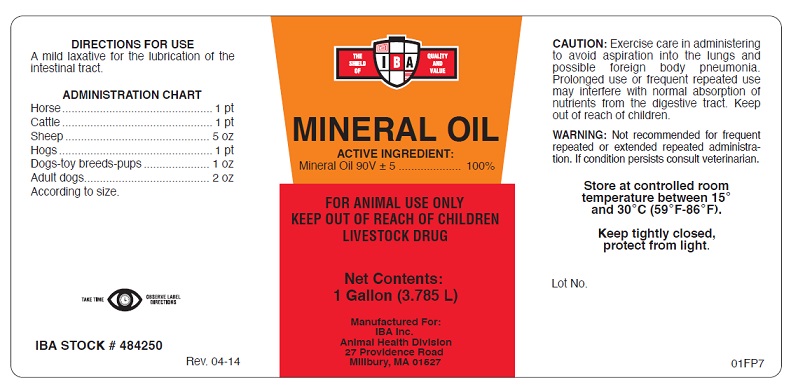 DRUG LABEL: Mineral Oil
NDC: 29983-2552 | Form: OIL
Manufacturer: IBA, Inc.
Category: animal | Type: OTC ANIMAL DRUG LABEL
Date: 20251207

ACTIVE INGREDIENTS: Light Mineral Oil 3.785 L/3.785 L

MINERAL OIL LIGHT

ACTIVE INGREDIENT

Mineral Oil 90V + 5 .........................100.0%

FOR ANIMAL USE ONLY

KEEP OUT OF REACH OF CHILDREN

LIVESTOCK DRUG

DIRECTIONS FOR USE

A mild laxative for lubrication of the intestinal tract.

ADMINISTRATION CHART

Horse ................................................ 1 pt
Cattle ................................................ 1 pt
Sheep ............................................... 5 oz
Hogs ................................................. 1 pt
Dogs-toy breeds-pups ........................ 1 oz
Adult dogs ........................................ 2 oz
According to size.

TAKE TIME OBSERVE LABEL DIRECTIONS

CAUTION

Exercise care in administering to avoid aspiration into the lungs and possible foreign body pneumonia. Prolonged use or frequent repeated use may interfere with normal absorption of nutrients from the digestive tract. Keep out of reach of children.

WARNING

Not recommended for frequent repeated or extended repeated administration. If condition persists consult veterinarian.

STORAGE AND HANDLING

Store at controlled room temperature between 15o and 30oC (59oF-86oF)

Keep tightly closed, protect from light.